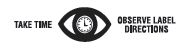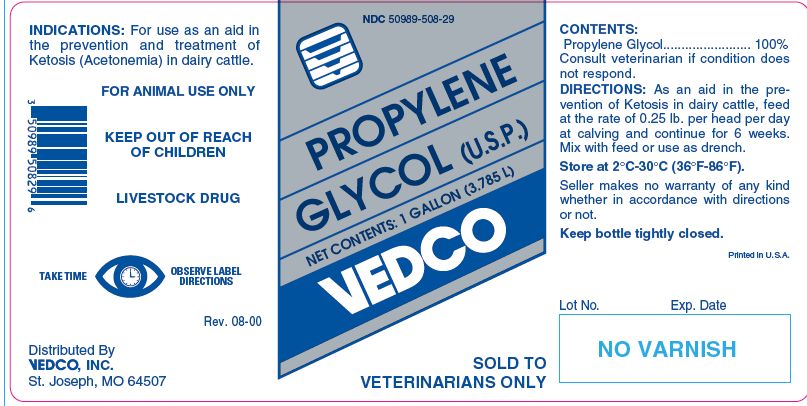 DRUG LABEL: PROPYLENE GLYCOL
NDC: 50989-508 | Form: LIQUID
Manufacturer: Vedco, Inc.
Category: animal | Type: OTC ANIMAL DRUG LABEL
Date: 20241029

ACTIVE INGREDIENTS: PROPYLENE GLYCOL 1034.2 g/1 L

PROPYLENE GLYCOL (U.S.P.)

WHEN USING

SOLD TO VETERINARIANS ONLY

INDICATIONS:

For use as an aid in the prevention and treatment of Ketosis (Acetonemia) in dairy cattle.

KEEP OUT OF REACH OF CHILDREN

FOR ANIMAL USE ONLY

KEEP OUT OF REACH OF CHILDREN

LIVESTOCK DRUG

CONTENTS:

Propylene Glycol........................ 100%
Consult veterinarian if condition does not respond.

DIRECTIONS:

As an aid in the prevention of Ketosis in dairy cattle, feed at the rate of 0.25 lb. per head per day at calving and continue for 6 weeks. Mix with feed or use as drench.

STORAGE AND HANDLING

Store at 2°C-30°C (36°F-86°F).

Seller makes no warranty of any kind whether in accordance with directions or not.

Keep bottle tightly closed.

NET CONTENTS:

1 GALLON (3.785 L)

INFORMATION FOR OWNERS/CAREGIVERS

Printed in U.S.A.

Distributed By
VEDCO, INC.
St. Joseph, MO 64507